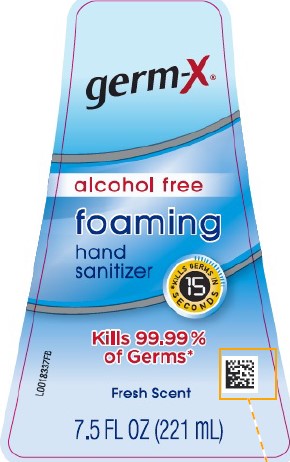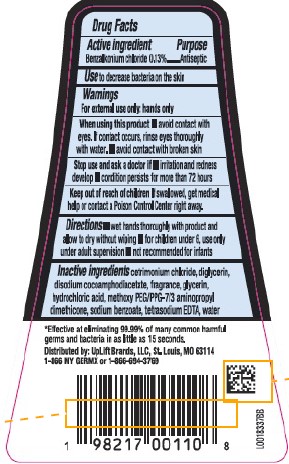 DRUG LABEL: Foaming Hand Sanitizer
NDC: 83986-118 | Form: LIQUID
Manufacturer: UpLift Brands LLC
Category: otc | Type: HUMAN OTC DRUG LABEL
Date: 20251113

ACTIVE INGREDIENTS: BENZALKONIUM CHLORIDE 1.3 mg/1 mL
INACTIVE INGREDIENTS: CETRIMONIUM CHLORIDE; DIGLYCERIN; DISODIUM COCOAMPHODIACETATE; GLYCERIN; HYDROCHLORIC ACID; METHOXY PEG/PPG-7/3 AMINOPROPYL DIMETHICONE; SODIUM BENZOATE; EDETATE SODIUM; WATER

Germ-X 118.001/118.401/118AE-AF
Foaming Hand Sanitizer

Active ingredient

Benzalkonium Chloride 0.13%

Purpose

Antiseptic

Use

to decrease bacteria on the skin

Warnings

For external use only: hands only

When using this product

- avoid contact with eyes. If contact occurs, rinse thoroughly with water.
- avoid contact with broken skin

Stop use and ask a doctor if

- if irritation and redness develops
- condition persists for more than 72 hours

Keep out of reach of children.

If swallowed get medical help or contact a Poison Control Center right away.

Directions

- wet hands thoroughly with product and allow to dry without wiping
- for children under 6, use only under adult supervision
- not recommended for infants

Inactive ingredients

cetrimonium chloride, diglycerin, disodium cocoamphodiacetate, fragrance, glycerin, hydrochloric acid, methoxy PEG/PPG-7/3 aminopropyl dimethicone, sodium benzoate, tetrasodium EDTA, water

Claims

*Effective at eliminating 99.99% of many common harmful germs and bacteria in as little as 15 seconds.

Adverse reactions

DISTRIBUTED BY:

UPLIFT BRANDS, LLC

ST. LOUIS, MO 63114

1-866 MY GERMX or 1-866-694-3769

Principal display panel

germ-X®

ALCOHOL FREE

FOAMING

HAND SANITIZER

Kills 99.99% of Germs*

*KILLS GERMS IN 15 SECONDS

Fresh Scent

7.5 FL OZ (221 mL)